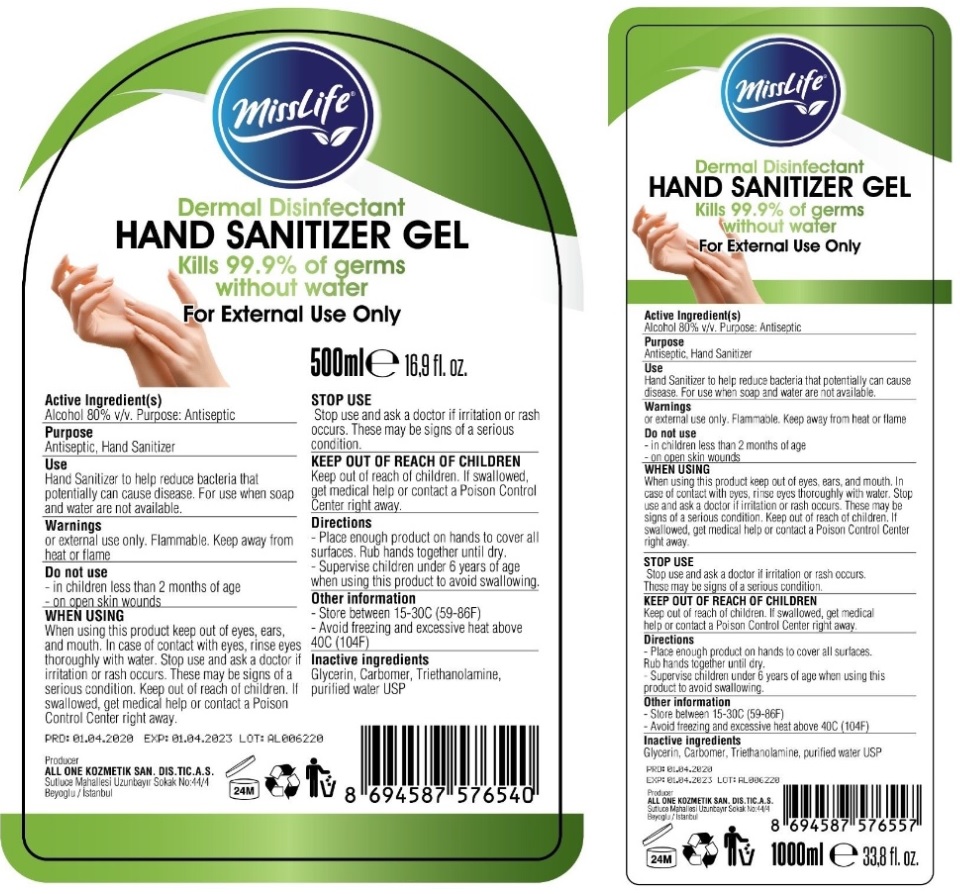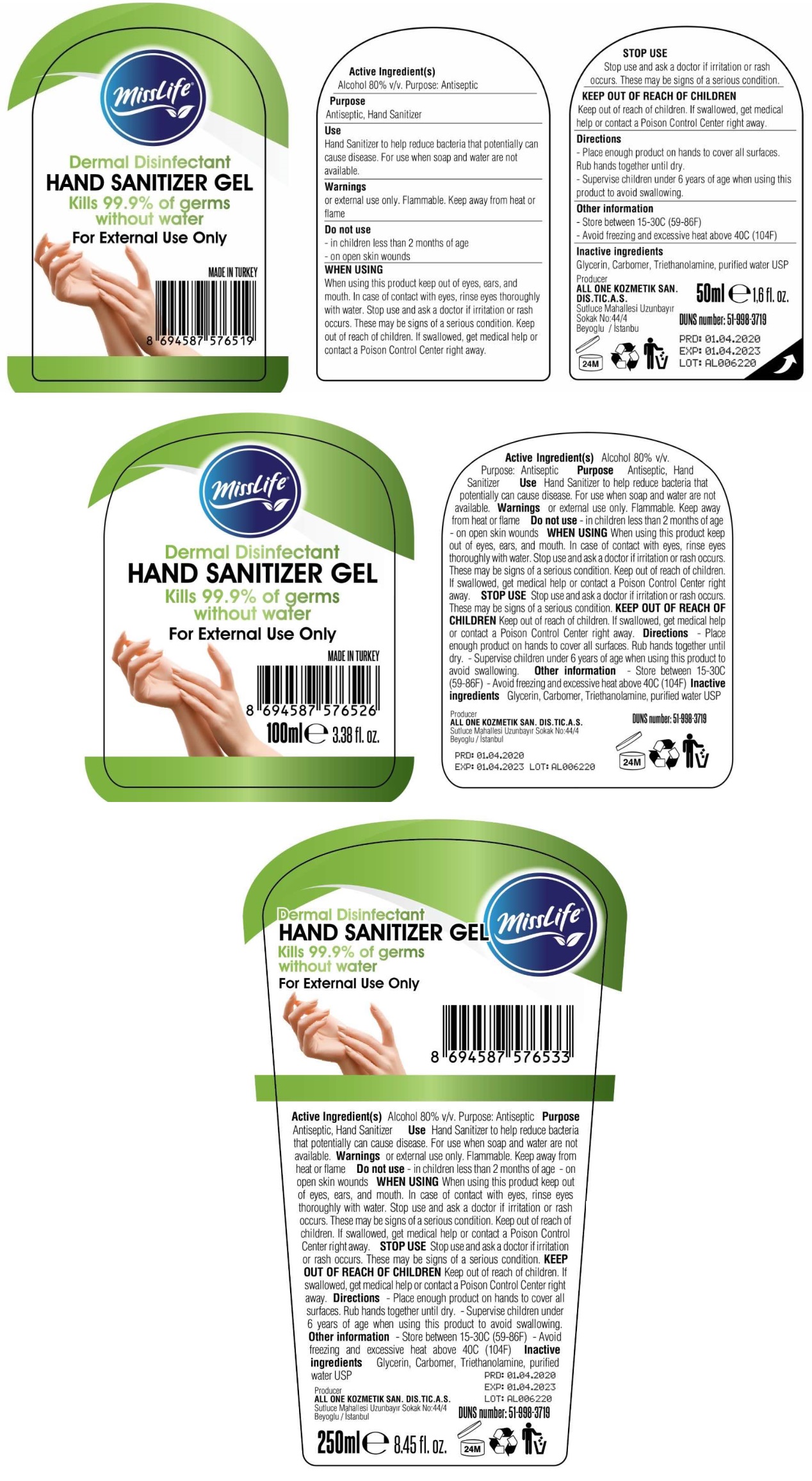 DRUG LABEL: missLife HAND SANITIZER Gel
NDC: 75348-312 | Form: GEL
Manufacturer: ALL ONE KOZMETIK SANAYI DIS TICARET ANONIM SIRKETI
Category: otc | Type: HUMAN OTC DRUG LABEL
Date: 20200624

ACTIVE INGREDIENTS: ALCOHOL 80 mL/100 mL
INACTIVE INGREDIENTS: GLYCERIN; CARBOMER HOMOPOLYMER, UNSPECIFIED TYPE; TROLAMINE; WATER

missLife HAND SANITIZER GEL

Active Ingredient(s)

Alcohol 80% v/v.

Purpose:

Antiseptic

Use

Hand Sanitizer to help reduce bacteria that potentially can cause disease. For use when soap and water are not available.

Warnings

For external use only. Flammable. Keep away from heat or flame

Do not use

- in children less than 2 months of age

- on open skin wounds

WHEN USING

When using this product keep out of eyes, ears, and mouth. In case of contact with eyes, rinse eyes thoroughly with water. Stop use and ask a doctor if irritation or rash occurs. These may be signs of a serious condition. Keep out of reach of children. If swallowed, get medical help or contact a Poison Control Center right away.

STOP USE

Stop use and ask a doctor if irritation or rash occurs. These may be signs of a serious condition.

Keep out of reach of children. If swallowed, get medical help or contact a Poison Control Center right away.

Directions

- Place enough product on hands to cover all surfaces. Rub hands together until dry.

- Supervise children under 6 years of age when using this product to avoid swallowing.

Other information

- Store between 15-30C (59-86F)

- Avoid freezing and excessive heat above 40C (104F)

Inactive ingredients

Glycerin, Carbomer, Triethanolamine, purified water USP

Dermal Disinfectant

Kills 99.9% of germs without water

MADE IN TURKEY

Producer

ALL ONE KOZMETIK SAN. DIS. TIC. A.S.

Sutluce Mahallesi Uzunbayir

Sokak No:44/4

Beyoglu / Istanbu